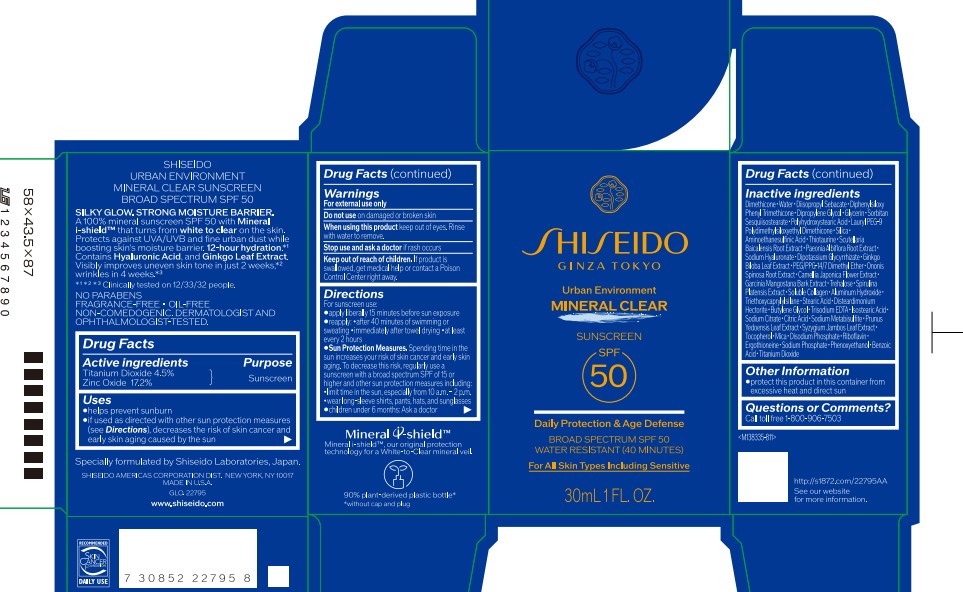 DRUG LABEL: SHISEIDO URBAN ENVIRONMENT MINERAL CLEAR SUNSCREEN
NDC: 58411-951 | Form: LOTION
Manufacturer: Shiseido Americas Corporation
Category: otc | Type: HUMAN OTC DRUG LABEL
Date: 20260223

ACTIVE INGREDIENTS: TITANIUM DIOXIDE 1.38 g/30 mL; ZINC OXIDE 5.28 g/30 mL
INACTIVE INGREDIENTS: DIMETHICONE; WATER; DIISOPROPYL SEBACATE; DIPHENYLSILOXY PHENYL TRIMETHICONE; DIPROPYLENE GLYCOL; GLYCERIN; SORBITAN SESQUIISOSTEARATE; POLYHYDROXYSTEARIC ACID (2300 MW); LAURYL PEG-9 POLYDIMETHYLSILOXYETHYL DIMETHICONE; SILICA; AMINOETHANESULFINIC ACID; THIOTAURINE; SCUTELLARIA BAICALENSIS ROOT; PAEONIA ALBIFLORA FLOWER; SODIUM HYALURONATE; DIPOTASSIUM GLYCYRRHIZATE; GINKGO BILOBA LEAF; PEG/PPG-14/7 DIMETHYL ETHER; ONONIS SPINOSA ROOT; CAMELLIA JAPONICA FLOWER; GARCINIA MANGOSTANA BARK; TREHALOSE; SPIRULINA PLATENSIS; ALUMINUM HYDROXIDE; TRIETHOXYCAPRYLYLSILANE; STEARIC ACID; DISTEARDIMONIUM HECTORITE; BUTYLENE GLYCOL; TRISODIUM EDTA; ISOSTEARIC ACID; SODIUM CITRATE; CITRIC ACID; SODIUM METABISULFITE; PRUNUS X YEDOENSIS LEAF; SYZYGIUM JAMBOS LEAF; TOCOPHEROL; MICA; DISODIUM PHOSPHATE; RIBOFLAVIN; ERGOTHIONEINE; SODIUM PHOSPHATE; PHENOXYETHANOL; BENZOIC ACID

SHISEIDO URBAN ENVIRONMENT MINERAL CLEAR SUNSCREEN

Drug Facts

Active Ingredients | Purpose
Titanium Dioxide 4.5% | Sunscreen
Zinc Oxide 17.2% | Sunscreen

Uses

- helps prevent sunburn
- if used as directed with other sun protection measures (see Directions), decreases the risk of skin cancer and early skin aging cause by the sun

Warnings

For external use only

Do not use on damaged or broken skin

When using this product keep out of eyes. Rinse with water to remove.

Stop use and ask a doctor if rash occurs

Keep out of reach of children. If product is swallowed, get medical help or contact a Poison Control Center right away.

Directions

For sunscreen use:

- apply liberally 15 minutes before sun exposure
- reapply: • after 40 minutes of swimming or sweating • immediately after towel drying • at least every 2 hours
- Sun Protection Measures. Spending time in the sun increases your risk of skin cancer and early skin aging. To decrease this risk, regularly use a sunscreen with a broad spectrum SPF of 15 or higher and other sun protection measures including:

• limit time in the sun, especially from 10 a.m. - 2 p.m.

• wear long-sleeve shirts, pants, hats, and sunglasses

- children under 6 months: Ask a doctor

INACTIVE INGREDIENT

DIMETHICONE･WATER･DIISOPROPYL SEBACATE･DIPHENYLSILOXY PHENYL TRIMETHICONE･DIPROPYLENE GLYCOL･GLYCERIN･SORBITAN SESQUIISOSTEARATE･POLYHYDROXYSTEARIC ACID･LAURYL PEG-9 POLYDIMETHYLSILOXYETHYL DIMETHICONE･SILICA･AMINOETHANESULFINIC ACID･THIOTAURINE･SCUTELLARIA BAICALENSIS ROOT EXTRACT･PAEONIA ALBIFLORA ROOT EXTRACT･SODIUM HYALURONATE･DIPOTASSIUM GLYCYRRHIZATE･GINKGO BILOBA LEAF EXTRACT･PEG/PPG-14/7 DIMETHYL ETHER･ONONIS SPINOSA ROOT EXTRACT･CAMELLIA JAPONICA FLOWER EXTRACT･GARCINIA MANGOSTANA BARK EXTRACT･TREHALOSE･SPIRULINA PLATENSIS EXTRACT･SOLUBLE COLLAGEN･ALUMINUM HYDROXIDE･TRIETHOXYCAPRYLYLSILANE･STEARIC ACID･DISTEARDIMONIUM HECTORITE･BUTYLENE GLYCOL･TRISODIUM EDTA･ISOSTEARIC ACID･SODIUM CITRATE･CITRIC ACID･SODIUM METABISULFITE･PRUNUS YEDOENSIS LEAF EXTRACT･SYZYGIUM JAMBOS LEAF EXTRACT･TOCOPHEROL･MICA･DISODIUM PHOSPHATE･RIBOFLAVIN･ERGOTHIONEINE･SODIUM PHOSPHATE･PHENOXYETHANOL･BENZOIC ACID･TITANIUM DIOXIDE･

Other information

- protect this productt in this container from excessive heat and direct sun

Questions or Comments?

Call toll free 1-800-906-7503

PRINCIPAL DISPLAY PANEL - 30 mL Bottle

SHISEIDO

Ginza Tokyo

Urban Environment

MINERAL CLEAR

Sunscreen

SPF 50

Daily Protection & Age Defense

BROAD SPECTRUM SPF 50

WATER RESISTANT (40 MINUTES)

For All Skin Types Including Sensitive

30mL 1 FL. OZ.